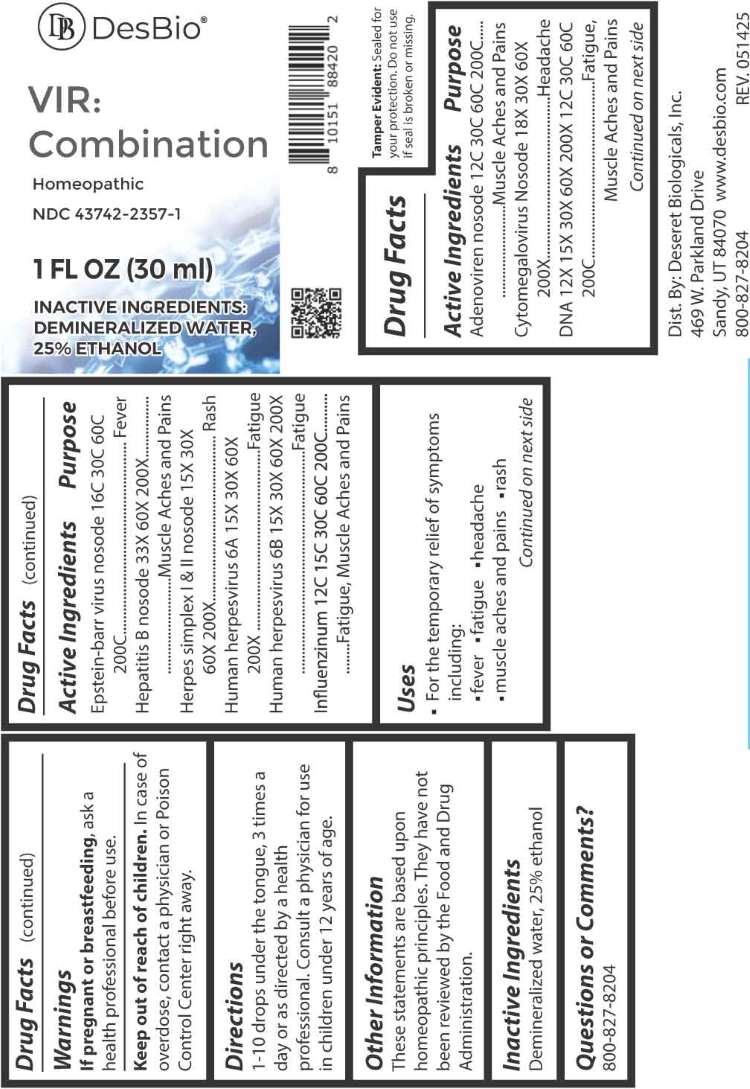 DRUG LABEL: VIR Combination
NDC: 43742-2357 | Form: LIQUID
Manufacturer: Deseret Biologicals, Inc.
Category: homeopathic | Type: HUMAN OTC DRUG LABEL
Date: 20260226

ACTIVE INGREDIENTS: HUMAN ADENOVIRUS E SEROTYPE 4 STRAIN CL-68578 ANTIGEN 12 [hp_C]/1 mL; HUMAN HERPESVIRUS 5 18 [hp_X]/1 mL; HERRING SPERM DNA 12 [hp_X]/1 mL; HUMAN HERPESVIRUS 4 16 [hp_C]/1 mL; HEPATITIS B VIRUS 33 [hp_X]/1 mL; HUMAN HERPESVIRUS 1 15 [hp_X]/1 mL; HUMAN HERPESVIRUS 2 15 [hp_X]/1 mL; HUMAN HERPESVIRUS 6 15 [hp_X]/1 mL; INFLUENZA A VIRUS A/VICTORIA/4897/2022 IVR-238 (H1N1) ANTIGEN (FORMALDEHYDE INACTIVATED) 12 [hp_C]/1 mL; INFLUENZA A VIRUS A/THAILAND/8/2022 IVR-237 (H3N2) ANTIGEN (FORMALDEHYDE INACTIVATED) 12 [hp_C]/1 mL; INFLUENZA B VIRUS B/AUSTRIA/1359417/2021 BVR-26 WHOLE 12 [hp_C]/1 mL; INFLUENZA B VIRUS B/PHUKET/3073/2013 BVR-1B WHOLE 12 [hp_C]/1 mL
INACTIVE INGREDIENTS: WATER; ALCOHOL

DRUG FACTS:

ACTIVE INGREDIENTS:

Adenoviren Nosode 12C, 30C, 60C, 200C, Cytomegalovirus Nosode 18X, 30X, 60X, 200X, DNA 12X, 15X, 30X, 60X, 200X, 12C, 30C, 60C, 200C, Epstein-Barr Virus Nosode 16C, 30C, 60C, 200C, Hepatitis B Nosode 33X, 60X, 200X, Herpes Simplex I Nosode 15X, 30X, 60X, 200X, Herpes Simplex II Nosode 15X, 30X, 60X, 200X, Human Herpesvirus 6A 15X, 30X, 60X, 200X, Human Herpesvirus 6B 15X, 30X, 60X, 200X, Influenzinum 12C, 15C, 30C, 60C, 200C.

PURPOSE

Adenoviren Nosode – Muscle Aches and Pains, Cytomegalovirus Nosode - Headache, DNA – Fatigue, Muscle Aches and Pains, Epstein-Barr Virus Nosode - Fever, Hepatitis B Nosode – Muscle Aches and Pains, Herpes Simplex I Nosode - Rash, Herpes Simplex II Nosode - Rash, Human Herpesvirus 6A - Fatigue, Human Herpesvirus 6B - Fatigue, Influenzinum – Fatigue, Muscle Aches and Pains

USES:

• For the temporary relief of symptoms including:

• fever • fatigue • headache • muscle aches and pains • rash

These statements are based upon homeopathic principles. They have not been reviewed by the Food and Drug Administration.

WARNINGS:

If pregnant or breastfeeding, ask a health professional before use.

Keep out of reach of children. In case of overdose, contact a physician or Poison Control Center right away.

Tamper Evident: Sealed for your protection. Do not use if seal is broken or missing.

KEEP OUT OF REACH OF CHILDREN:

In case of overdose, contact a physician or Poison Control Center right away.

DIRECTIONS:

1-10 drops under the tongue, 3 times a day or as directed by a health professional. Consult a physician for use in children under 12 years of age.

INACTIVE INGREDIENTS:

Demineralized water, 25% ethanol

QUESTIONS:

Dist. By: Deseret Biologicals, Inc.

469 W. Parkland Drive

Sandy, UT 84070

www.desbio.com

800-827-8204

PACKAGE LABEL DISPLAY:

DesBio

VIR:Combination

Homeopathic

NDC 43742-2357-1

1 FL OZ (30 ml)